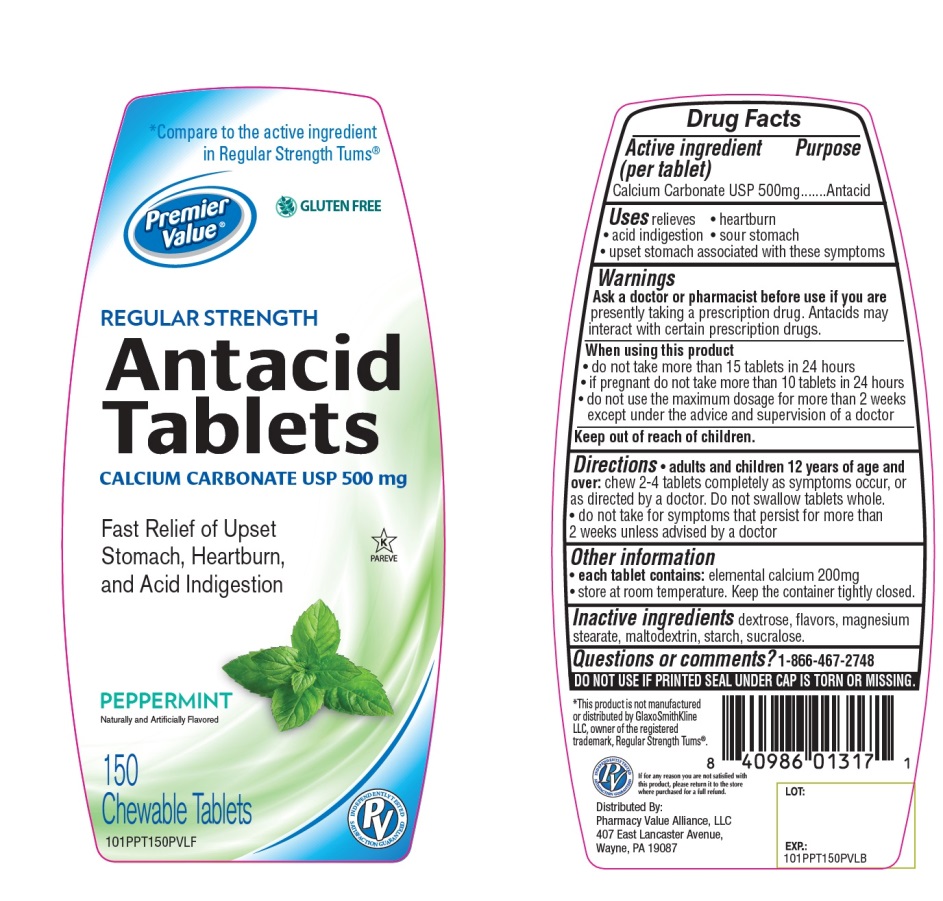 DRUG LABEL: Premier Value Regular Strength Chewable Antacid Peppermint
NDC: 68016-665 | Form: TABLET, CHEWABLE
Manufacturer: Chain Drug Consortium, LLC
Category: otc | Type: HUMAN OTC DRUG LABEL
Date: 20241025

ACTIVE INGREDIENTS: CALCIUM CARBONATE 500 mg/1 1
INACTIVE INGREDIENTS: DEXTROSE, UNSPECIFIED FORM; MAGNESIUM STEARATE; MALTODEXTRIN; STARCH, CORN; SUCRALOSE

Regular Strength Antacid tablets Drug Facts

Active ingredient

Calcium Carbonate USP 500mg

Purpose

Antacid

Uses

relieves:

• heartburn

• sour stomach

• acid indigestion

• upset stomach associated with these symptoms

Warnings

Ask a doctor or pharmacist before use if you are taking a prescription drug. Antacids may interact with certain prescription drugs.

When using this product

• do not take more than 15 tablets in 24 hours

• id pregnant do not take more than 10 tablets in 24 hours

• do not use the maximum dosage for more than 2 weeks except under the advice and supervision of a doctor.

Directions

• adults and children 12 years of age and over: chew 2-4 tablets completely as symptoms occur, or as directed by a doctor. Do not swallow tablets whole.

• do not take for symptoms that persist for more than 2 weeks unless advised by a doctor.

Other Information

each tablet contains: elemental calcium 200mg

• Store at room temperature. Keep the container tightly closed

Inactive ingredients

dextrose, flavors, magnesium stearate, maltodextrin, starch, sucralose.

Questions or comments?

1-866-467-2748

Package/Label Principal Display Panel

Compare to the active ingredient in Regular Strength Tums®*

Premier Value®

REGULAR STRENGTH

Antacid Tablets

CALCIUM CARBONATE USO 500mg

For Fast Relief of Heartburn, Acid Indigestion & Upset Stomach

PEPPERMINT

Naturally and Artificially Flavored

150 Chewable Tablets

Distributed by

Pharmacy Value Alliance, LLC

407 East Lancaster Avenue,

Wayne, PA 19087

*This product is not manufactured or distributed by GlaxoSmithKline LLC, the owner of the registered trademark, Regular Strength Tums®

SAFETY SEALED: DO NOT USE IF PRINTED SEAL UNDER CAP IS TORN OR MISSING